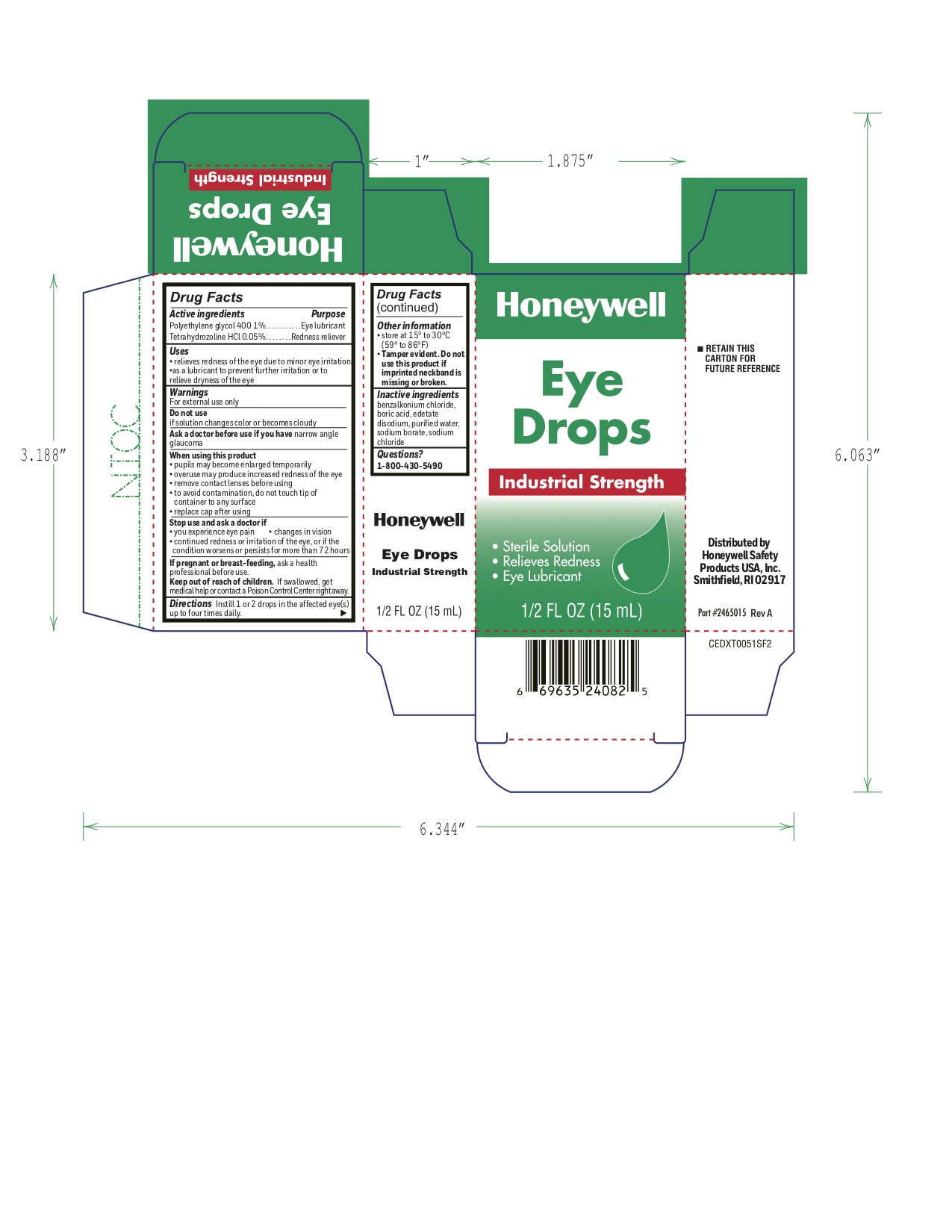 DRUG LABEL: Industrial Strength Eye Drops
NDC: 0498-0162 | Form: SOLUTION/ DROPS
Manufacturer: Honeywell Safety Products USA, INC
Category: otc | Type: HUMAN OTC DRUG LABEL
Date: 20240122

ACTIVE INGREDIENTS: TETRAHYDROZOLINE HYDROCHLORIDE 0.05 g/100 mL; POLYETHYLENE GLYCOL 400 1 g/100 mL
INACTIVE INGREDIENTS: BENZALKONIUM CHLORIDE; BORIC ACID; EDETATE DISODIUM; WATER; SODIUM BORATE; SODIUM CHLORIDE

0498-0162: Industrial Eye Drops

Industrial Strength Eye Drops Active ingredients

Polyethylene glycol 400 1%

Tetrahydrozoline HCl 0.05%

Industrial Strength Eye Drops Purpose

Eye lubricant

Redness reliever

Industrial Strength Eye Drops Uses

- relieves redness of the eye due to minor eye irritations
- as a lubricant to prevent further irritation or to relieve dryness of the eye

Industrial Strength Eye drops Warnings

For external use only

Do not use

if solution changes color or becomes cloudy

Ask a doctor before use if you have

narrow angle glaucoma

When using this product

- pupils may become enlarged temporarily
- overuse may produce increased redness of the eye
- remove contact lenses before using
- to avoid contamination, do not touch tip of container to any surface
- replace cap after using

Stop use and ask a doctor if

- you experience eye pain
- changes in vision
- continued redness or irritation of the eye, or if the condition worsens or persists for more than 72 hours

If pregnant or breast-feeding

ask a health professional before use.

Keep out of reach of children

If swallowed, get medical help or contact a Poison Control Center right away.

Industrial Strength Eye Drops Directions

Instill 1 or 2 drops in the affected eye(s) up to four times daily.

Industrial Strength Eye Drops Other information

store at 15° to 30°C (59° to 86°F)

Tamper evident. Do not use this product if imprinted neckband is missing or broken.

Industrial Strength Eye Drops Inactive ingredients

benzalkonium chloride, boric acid, edetate disodium, purified water, sodium borate, sodium chloride

Industrial Strength Eye Drops Questions?

1-800-430-5490